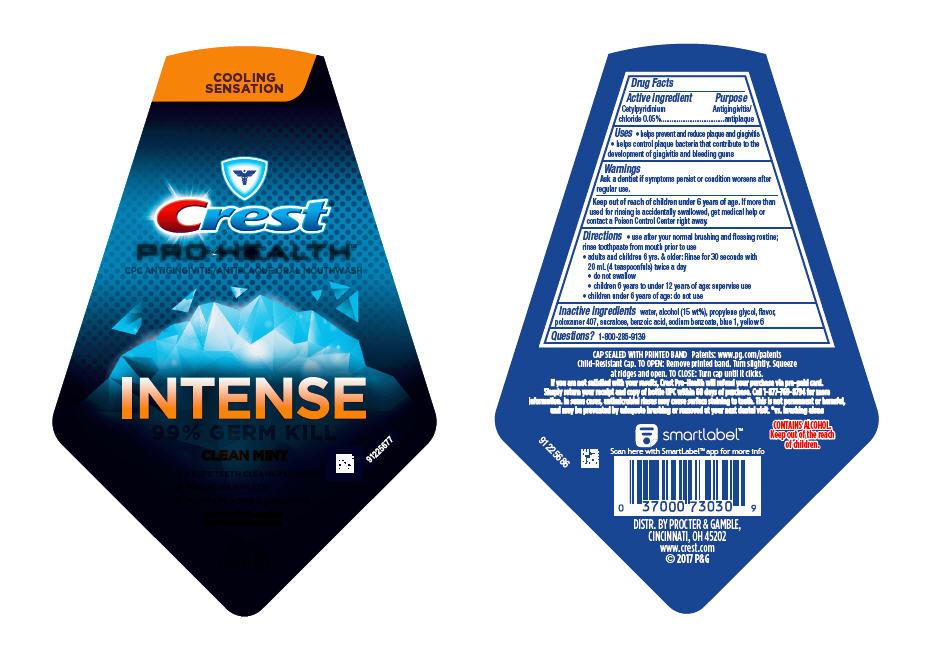 DRUG LABEL: Crest Pro-Health
NDC: 37000-479 | Form: RINSE
Manufacturer: The Procter & Gamble Manufacturing Company
Category: otc | Type: HUMAN OTC DRUG LABEL
Date: 20251217

ACTIVE INGREDIENTS: CETYLPYRIDINIUM CHLORIDE 0.05 g/1 mL
INACTIVE INGREDIENTS: PROPYLENE GLYCOL; POLOXAMER 407; WATER; FD&C YELLOW NO. 6; ALCOHOL; SUCRALOSE; SODIUM BENZOATE; FD&C BLUE NO. 1; BENZOIC ACID

Crest®
PRO-HEALTH™
INTENSE
CLEAN MINT

Drug Facts

Active ingredient

Cetylpyridinium chloride 0.05%

Purpose

Antigingivitis/antiplaque

Uses

- helps prevent and reduce plaque and gingivitis
- helps control plaque bacteria that contribute to the development of gingivitis and bleeding gums

Warnings

ASK DOCTOR

Ask a dentist if symptoms persist or condition worsens after regular use.

Keep out of reach of children under 6 years of age. If more than used for rinsing is accidentally swallowed, get medical help or contact a Poison Control Center right away.

Directions

- use after your normal brushing and flossing routine; rinse toothpaste from mouth prior to use
- adults and children 6 yrs. & older: Rinse for 30 seconds with 20 mL (4 teaspoonfuls) twice a day
  - do not swallow
  - children 6 years to under 12 years of age: supervise use
- children under 6 years of age: do not use

Inactive ingredients

water, alcohol (15 wt%), propylene glycol, flavor, poloxamer 407, sucralose, benzoic acid, sodium benzoate, blue 1, yellow 6

Questions?

1–800–285–9139

PRINCIPAL DISPLAY PANEL - 500 mL Bottle Label

COOLING

SENSATION

Crest®
PRO-HEALTH™
CPC ANTIGINGIVITIS/ANTIPLAQUE ORAL MOUTHWASH

INTENSE

99% GERM KILL

CLEAN MINT

- KEEPS TEETH CLEANER LONGER*
- FRESHENS BREATH
- FIGHTS PLAQUE & GINGIVITIS

See back for important

ingredient information.

500 mL

(16.9 FL OZ)